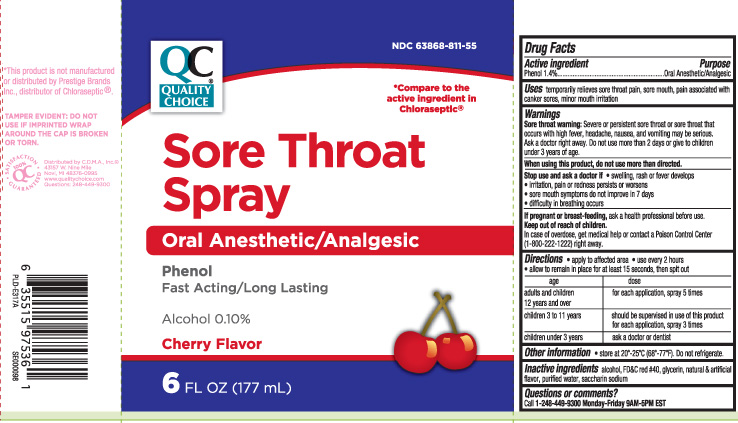 DRUG LABEL: Sore Throat
NDC: 63868-811 | Form: SPRAY
Manufacturer: QUALITY CHOICE (Chain Drug Marketing Association)
Category: otc | Type: HUMAN OTC DRUG LABEL
Date: 20240501

ACTIVE INGREDIENTS: PHENOL 1.4 g/100 mL
INACTIVE INGREDIENTS: ALCOHOL; FD&C RED NO. 40; GLYCERIN; WATER; SACCHARIN SODIUM

Drug Facts

Active ingredient

Phenol 1.4%

Purpose

Oral Anesthetic/Analgesic

Uses

temporarily relieves sore throat pain, sore mouth, pain associated with canker sores, minor mouth irritation

Warnings

Sore throat warning: Severe or persistent sore throat or sore throat that occurs with high fever, headache, nausea, and vomiting may be serious. Ask a doctor right away. Do not use more than 2 days or give to children under 3 years of age.

When using this product,

do not use more than directed.

Stop use and ask a doctor if

- swelling, rash or fever develops
- irritation, pain or redness persists or worsens
- sore mouth symptoms do not improve in 7 days
- difficulty in breathing occurs

If pregnant or breast-feeding,

ask a health professional before use.

Keep out of reach of children.

In case of overdose, get medical help or contact a Poison Control Center (1-800-222-1222) right away.

Directions

- apply to affected area
- use every 2 hours
- allow to remain in place for at least 15 seconds, then spit out

age | dose
adults and children 12 years and over | for each application, spray 5 times
children 3 to 11 years | should be supervised in use of this product for each application, spray 3 times
children under 3 years | ask a doctor or dentist

Other information

- store at 20º-25ºC (68º-77ºF). Do not refrigerate.

Inactive ingredients

alcohol, FD&C red #40, glycerin, natural & artificial flavor, purified water, saccharin sodium

Questions or comments?

Call 1-248-449-9300 Monday-Friday 9AM-5PM EST

Principal Display Panel

*Compare to the Active Ingredient in Chloraseptic®

Sore Throat Spray

Oral anesthetic/analgesic

Phenol

Fast acting/long lasting

Alcohol 0.10%

Cherry flavor

FL OZ (mL)

*This product is not manufactured or distributed by Prestige Brands Inc., distributor of Chloraseptic®.

TAMPER EVIDENT: DO NOT USE F IMPRINTED WRAP AROUND THE CAP IS BROKEN OR TORN.

Distributed by C.D.M.A., Inc.©

43157 W. Nine Mile

Novi, MI 48376-0995

www.qualitychoice.com

Package Label

Quality Choice Sore Throat Spray